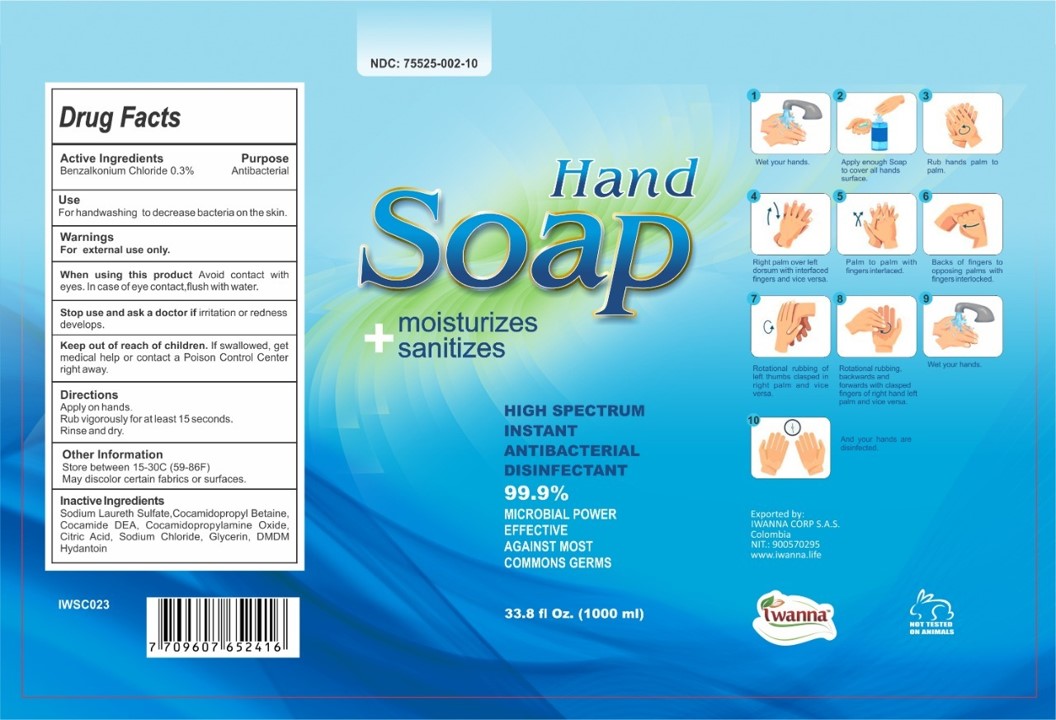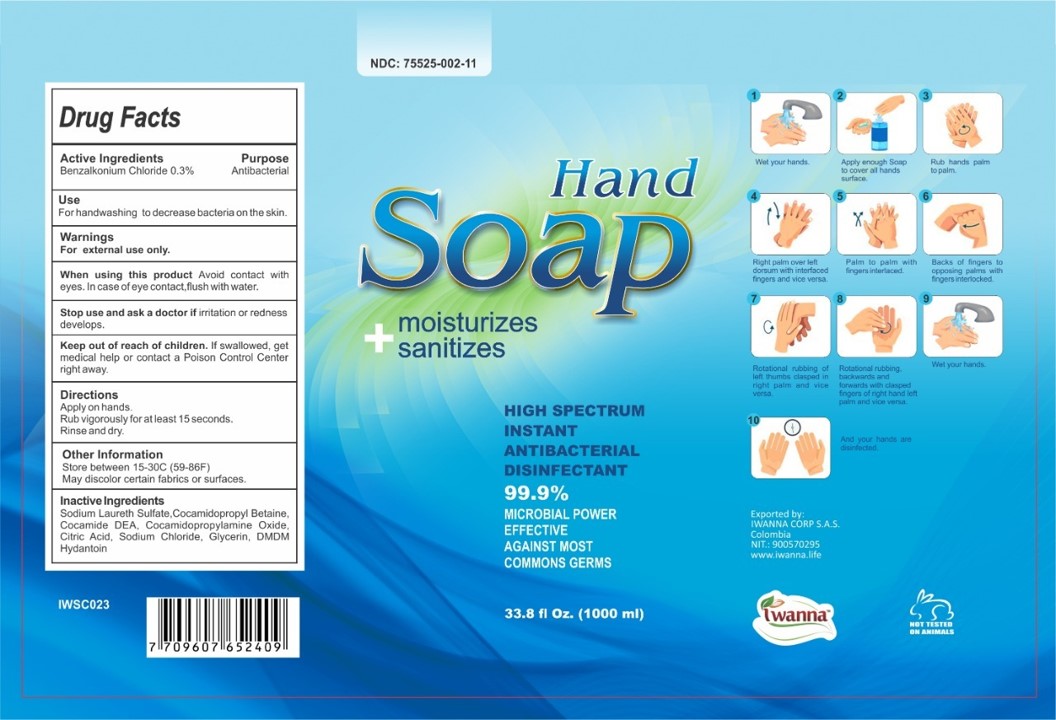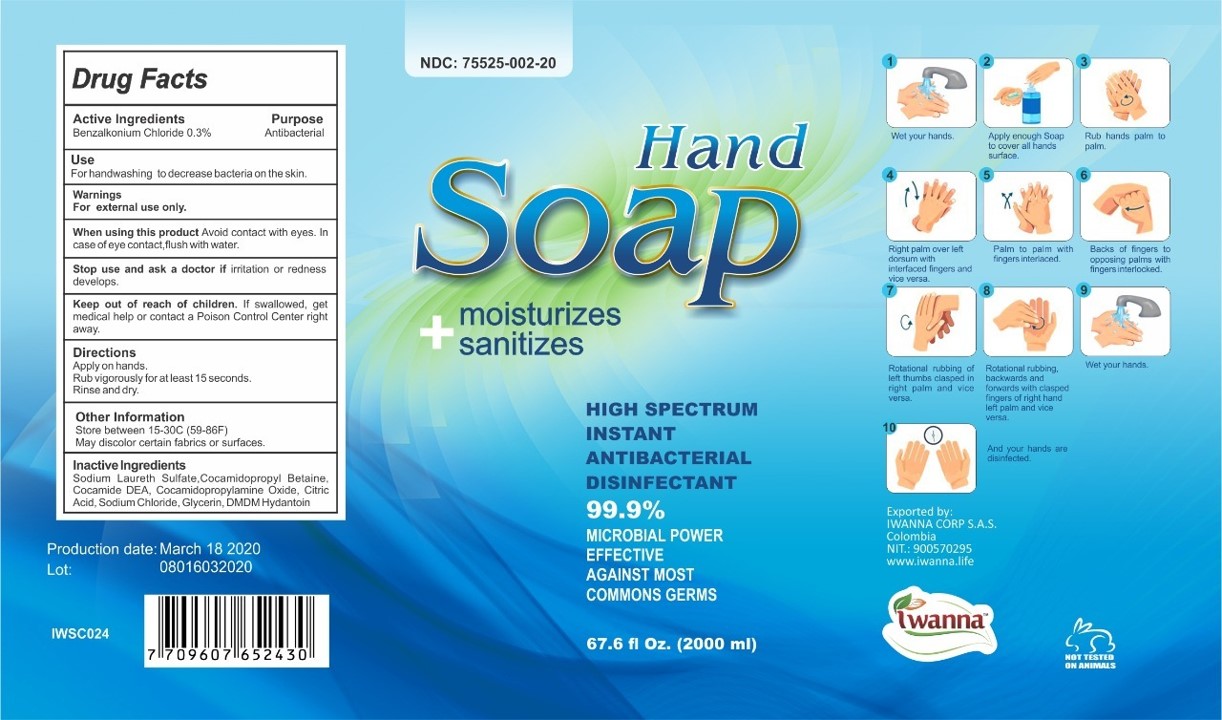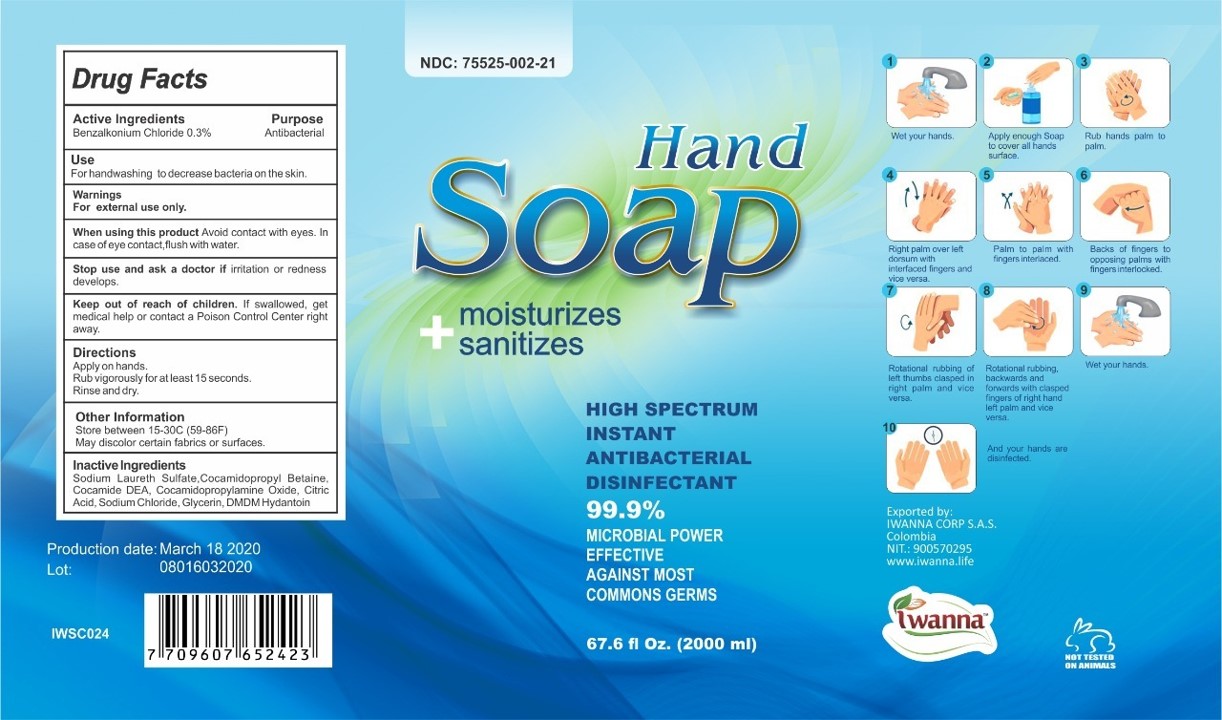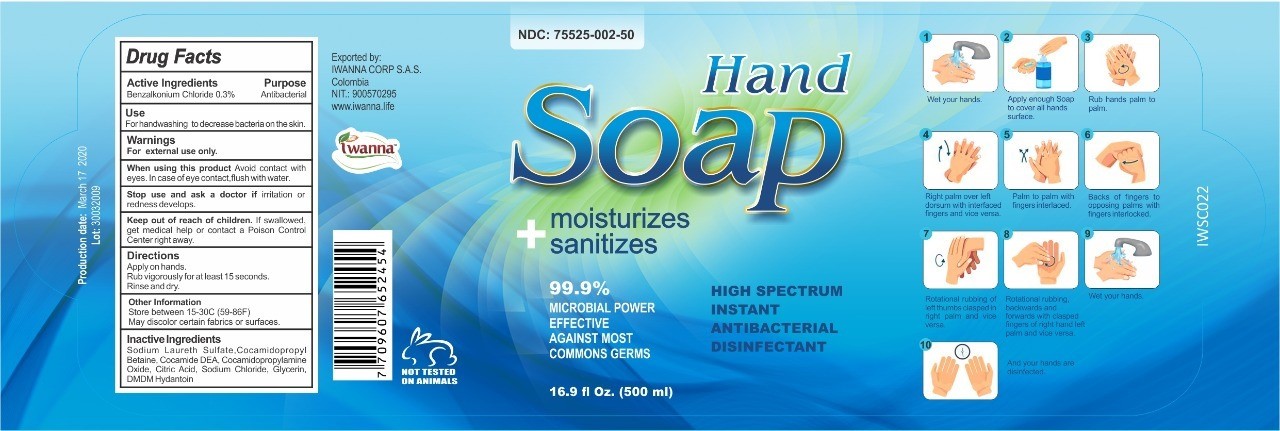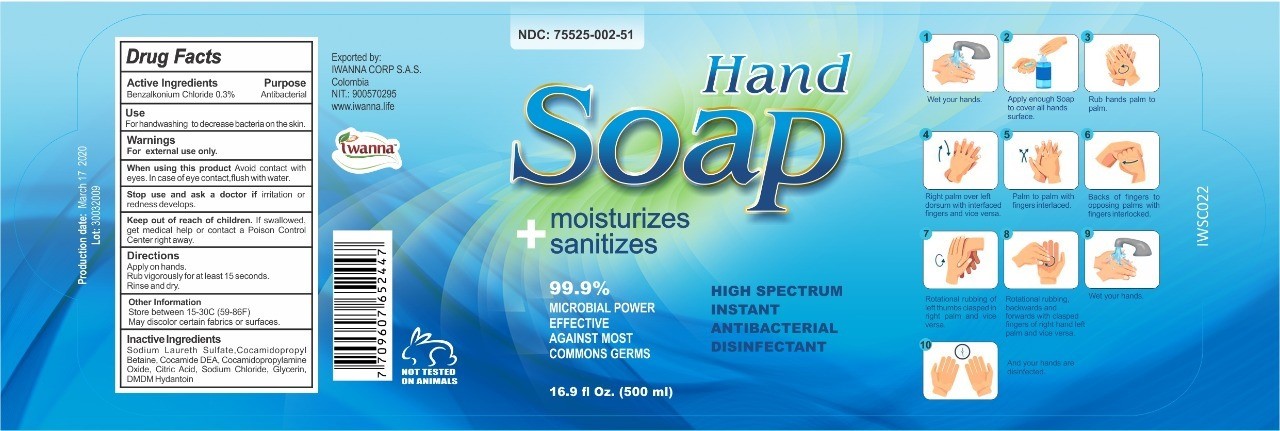 DRUG LABEL: Smells Clean
NDC: 75525-002 | Form: LIQUID
Manufacturer: IWANNA CORP SAS
Category: otc | Type: HUMAN OTC DRUG LABEL
Date: 20201202

ACTIVE INGREDIENTS: BENZALKONIUM CHLORIDE 0.3 g/100 mL
INACTIVE INGREDIENTS: COCAMIDOPROPYL BETAINE 2 mL/100 mL; COCO DIETHANOLAMIDE 0.5 mL/100 mL; SODIUM LAURETH SULFATE 10 mL/100 mL; WATER 83.92 mL/100 mL; SODIUM CHLORIDE 1 mL/100 mL; GLYCERIN 1 mL/100 mL; DMDM HYDANTOIN 0.1 mL/100 mL; COCAMIDOPROPYLAMINE OXIDE 1 mL/100 mL; CITRIC ACID MONOHYDRATE 0.18 mL/100 mL

HAND SOAP

Hand Antibacterial Soap

This is a Liquid Hand Soap

Active Ingredient POLYAMINOPROPYL BIGUANIDE

ACTIVE INGREDIENTS

BENZALKONIUM CHLORIDE 0.3%

Purpose: Antibacterial

PURPOSE

Purpose: Antibacterial

INDICATIONS AND USAGE

1.Wet your Hands

2.Apply enough soap to cover all hands surface

3. Rub hands palm to palm

4. Right hand over left dorsum with interfaced fingers and vice versa

5. Palm to palm with fingers interfaced

6. Backs on fingers to opposing palms with fingers interlocked

7.Rotational rubbing of left thumbs clasped in right palm and vice versa

8.Rotational rubbing of left thumbs clasped in right palm and vice versa

9. Wet and rinse your hands

10. And your hands are desinfected

WARNINGS

For external use only

When using this product avoid contact with eyes. In case of eye contact, flush with water

Stop use and ask a doctor if irritation or redness develops

Keep out of reach of children. If swallowed, get medical help or contact a Poison Control Center right away.

WHEN USING

When using this product avoid contact with eyes. In case of eye contact, flush with water

STOP USING

Stop use and ask a doctor if irritation or redness develops

DOSAGE AND ADMINISTRATION

Apply on Hands

Rub vigorously for at least 15 seconds

Rinse and dry

Keep out of reach of children. If swallowed, get medical help or contact a Poison Control Center right away.

STORAGE AND HANDLING

Store between 15-30 C (59-86 F)

May discolor certain fabrics or surfaces

INACTIVE INGREDIENT

Sodium Laureth Sulfate, Cocamidopropyl Betaine, Cocamide DEA, Cocamidopropylamine Oxyde, Citric Acid, Sodium Chloride, Glycerin, DMDM Hydantoin.

Package Label Principal Display

Hand Soap Antibacterial

High Spectrum

Instant Antibacterial

Desinfectant

Hand Soap 500 ml- Dispensing

Hand Soap

moisturizes+sanitizes

16.9 fl. oz (500 mL) NDC: 75525-002-50

Hand Soap 500 ml- Pump

Hand Soap

moisturizes+sanitizes

16.9 fl. oz (500 mL) NDC: 75525-002-51

Hand Soap 1000 ml- Dispenser

Hand Soap

moisturizes+sanitizes

33.8 fl. oz (1000 mL) NDC: 75525-002-10

Hand Soap 1000 ml- Pump

Hand Soap

moisturizes+sanitizes

33.8 fl. oz (1000 mL) NDC: 75525-002-11

Hand Soap 2000 ml- Dispenser

Hand Soap

moisturizes+sanitizes

67.6 fl. oz (2000 mL) NDC: 75525-002-20

Hand Soap 2000 ml- Pump

Hand Soap

moisturizes+sanitizes

67.6 fl. oz (2000 mL) NDC: 75525-002-21